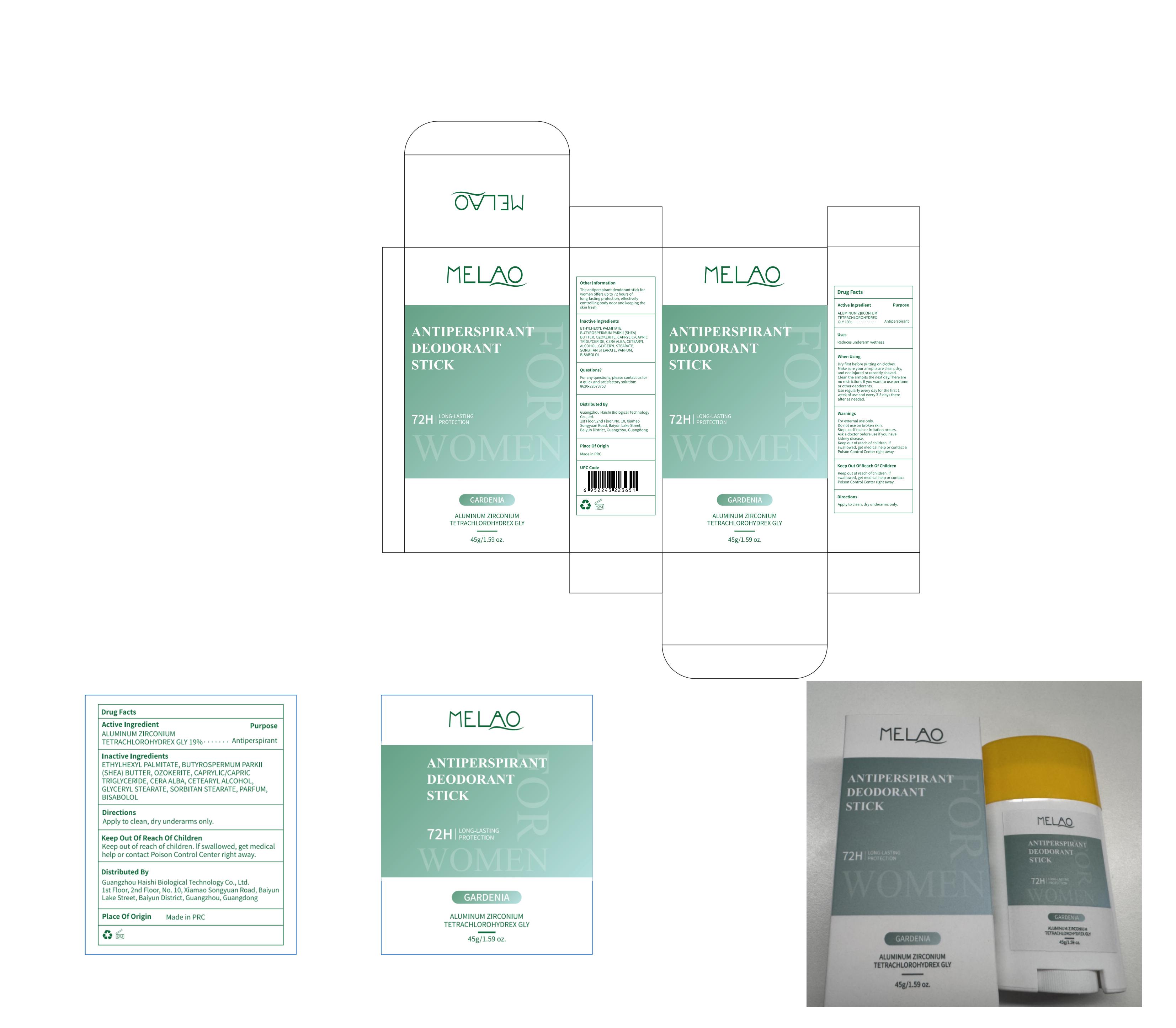 DRUG LABEL: MELAO Antiperspirant Deodorant Stick (gardenia)
NDC: 60771-0018 | Form: STICK
Manufacturer: Guangzhou Haishi Biological Technology Co., Ltd.
Category: otc | Type: HUMAN OTC DRUG LABEL
Date: 20250527

ACTIVE INGREDIENTS: ALUMINUM ZIRCONIUM TETRACHLOROHYDREX GLY 19 g/100 g
INACTIVE INGREDIENTS: GLYCERYL STEARATE; ETHYLHEXYL PALMITATE; SORBITAN STEARATE; CAPRYLIC/CAPRIC TRIGLYCERIDE; BISABOLOL; CETEARYL ALCOHOL

MELAO Antiperspirant Deodorant Stick (gardenia)

ACTIVE INGREDIENT

ALUMINUM ZIRCONIUM TETRACHLOROHYDREX GLY19%

PURPOSE

Antiperspirant

INDICATIONS AND USAGE

STEP1: Clean and thoroughly dry your skin.

STEP2: Twist the bottom of the product.

STEP3: Gently apply to the underarms or other desired areas.

WARNINGS

For external use only.

Ask a doctor before use if you have kidney disease.

if swallowed, get medical help or contact a Poison Control Center right away.

Stop use if rash or irritation occurs.

Do not use on broken skin.

Keep out of reach of children.

WHEN USING

Dry first before putting on clothes.Make sure your armpits are clean, dry,and not iniured or recently shaved.Clean the armpits the next day.Thereare no restrictions if you want to useperfume or other deodorants.

DOSAGE AND ADMINISTRATION

Use regularly every day for the first 1week of use and every 3-5 days thereafter as needed.

INACTIVE INGREDIENT

OZOKERITE10%
CETEARYL ALCOHOL4%
BUTYROSPERMUM PARKII (SHEA) BUTTER18%
CAPRYLIC/CAPRIC TRIGLYCERIDE10%
ETHYLHEXYL PALMITATE22.9%
GLYCERYL STEARATE4%
SORBITAN STEARATE4%
CERA ALBA6%
BISABOLOL0.1%
PARFUM2%